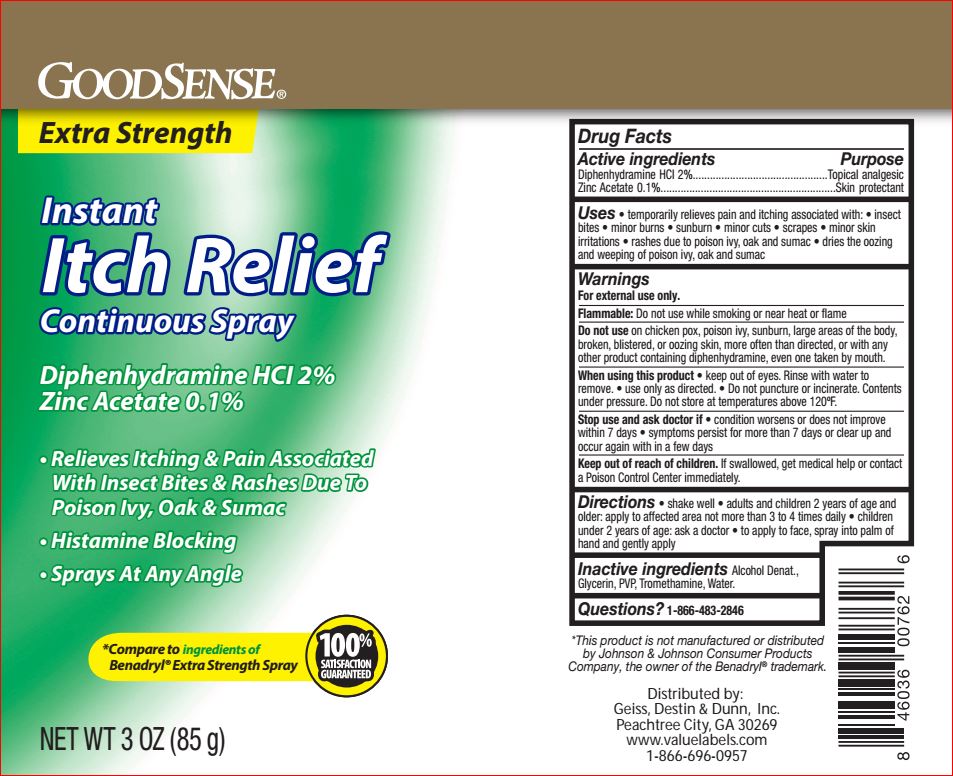 DRUG LABEL: Itch Relief
NDC: 50804-783 | Form: SPRAY
Manufacturer: Good Sense
Category: otc | Type: HUMAN OTC DRUG LABEL
Date: 20180808

ACTIVE INGREDIENTS: DIPHENHYDRAMINE HYDROCHLORIDE 2.0 g/100 g; ZINC ACETATE .10 g/100 g
INACTIVE INGREDIENTS: ALCOHOL; GLYCERIN; POVIDONE; WATER; TROMETHAMINE

Drug Facts

Active ingredients

Diphenhydramine HCl 2.0%

Zinc Acetate 0.10%

Purpose

Topical analgesic

Skin protectant

Uses

Temporarily relieves pain and itching associated with:

- insect bites
- minor burns
- sunburn
- minor cuts
- scrapes
- minor skin irritations
- rashes due to poison ivy, oak and sumac
- dries the oozing and weeping of poison ivy, oak and sumac

Warnings

For external use only.

Flammable - Do not use while smoking or near heat or flame

Do not use

- on large areas of the body, brocken, blistered, or oozing skin
- with any other product containing diphenhydramine, even one taken by mouth
- on chicken pox, poison ivy, sunburn

Stop use and ask a doctor if

- condition worsens
- symptoms last more than 7 days
- symptoms clear up and occur again in a few day

When using this product

keep out of eyes, rinse with water to remove
use only as directed.
do not puncture or incinerate. Contents under pressure. Do not store at temperatures above 120F

Keep out of reach of children.

If swallowed, get help or contact a Poison Control Center right away.

Directions

- shake well
- adults and children 2 years of age and older: apply to affected area not more than 3 to 4 times daily
- children under 2 years of age: ask a doctor
- to apply to face, spray into palm of hand and gently apply

Inactive ingredients

Alcohol Denat.
Glycerin
PVP
Tromethamine
Water